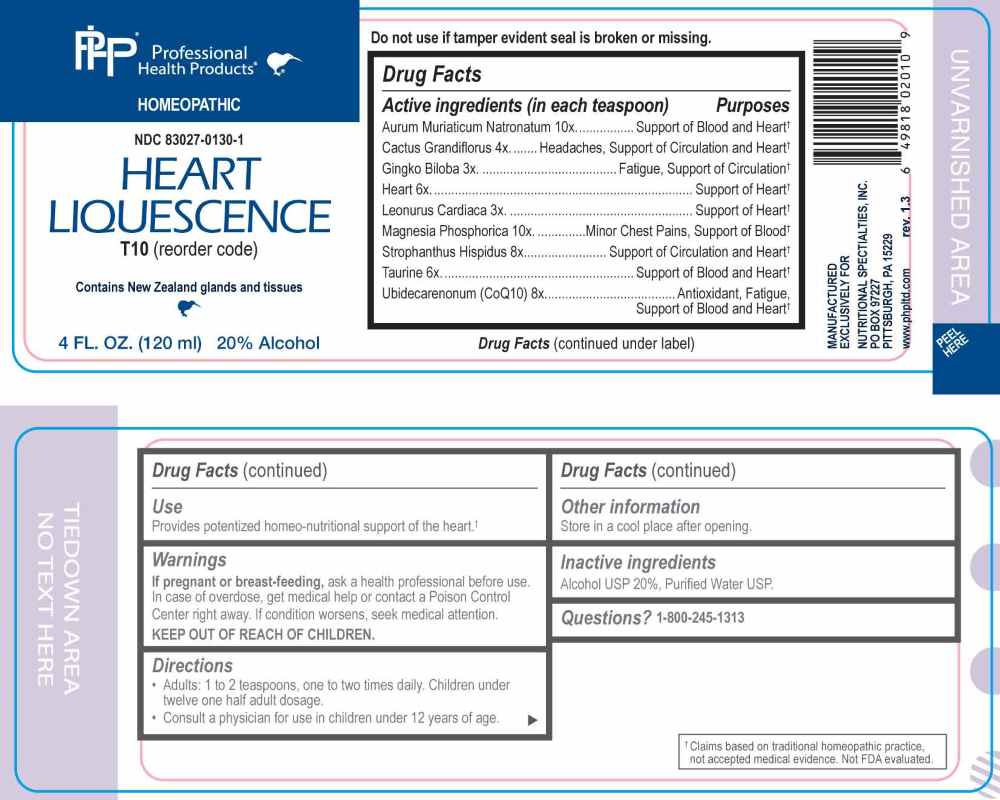 DRUG LABEL: Heart Liquescence
NDC: 83027-0130 | Form: LIQUID
Manufacturer: Nutritional Specialties, Inc.
Category: homeopathic | Type: HUMAN OTC DRUG LABEL
Date: 20251119

ACTIVE INGREDIENTS: GINKGO 3 [hp_X]/1 mL; LEONURUS CARDIACA WHOLE 3 [hp_X]/1 mL; SELENICEREUS GRANDIFLORUS STEM 4 [hp_X]/1 mL; BEEF HEART 6 [hp_X]/1 mL; TAURINE 6 [hp_X]/1 mL; STROPHANTHUS HISPIDUS SEED 8 [hp_X]/1 mL; UBIDECARENONE 8 [hp_X]/1 mL; SODIUM TETRACHLOROAURATE 10 [hp_X]/1 mL; MAGNESIUM PHOSPHATE, DIBASIC TRIHYDRATE 10 [hp_X]/1 mL
INACTIVE INGREDIENTS: WATER; ALCOHOL

DRUG FACTS:

ACTIVE INGREDIENTS:

Aurum Muriaticum Natronatum 10X, Cactus Grandiflorus 4X, Ginkgo Biloba 3X, Heart 6X, Leonurus Cardiaca 3X, Magnesia Phosphorica 10X, Strophanthus Hispidus 8X, Taurine 6X, Ubidecarenonum (CoQ10) 8X.

PURPOSE:

Aurum Muriaticum Natronatum – Support of Blood and Heart,† Cactus Grandiflorus – Headaches, Support of Circulation and Heart,† Ginkgo Biloba – Fatigue, Support of Circulation,† Heart – Support of Heart,† Leonurus Cardiaca – Support of Heart,† Magnesia Phosphorica – Minor Chest Pains, Support of Blood,† Strophanthus Hispidus – Support of Circulation and Heart,† Taurine – Support of Blood and Heart,† Ubidecarenonum (CoQ10) – Antioxidant, Fatigue, Support of Blood and Heart†

†Claims based on traditional homeopathic practice, not accepted medical evidence. Not FDA evaluated.

USE:

Provides potentized homeo-nutritional support of the heart.†

†Claims based on traditional homeopathic practice, not accepted medical evidence. Not FDA evaluated.

WARNINGS:

If pregnant or breast-feeding, ask a health professional before use.

In case of overdose, get medical help or contact a Poison Control Center right away.

If condition worsens, seek medical attention.

KEEP OUT OF REACH OF CHILDREN

Do not use if tamper evident seal is broken or missing.

Store in a cool place after opening

KEEP OUT OF REACH OF CHILDREN:

In case of overdose, get medical help or contact a Poison Control Center right away.

DIRECTIONS:

• Adults: 1 to 2 teaspoons, one to two times daily. Children under twelve one half adult dosage.

Consult a physician for use in children under 12 years of age.

INACTIVE INGREDIENTS:

Alcohol USP 20%, Purified Water USP.

QUESTIONS:

MANUFACTURED EXCLUSIVELY FOR

NUTRITIONAL SPECIALTIES, INC.

PO BOX 97227

PITTSBURG, PA 15229

www.phpltd.com

PACKAGE LABEL DISPLAY:

Professional

Health Products

HOMEOPATHIC

NDC 83027-0130-1

HEART LIQUESCENCE

4 FL. OZ (120 ml)